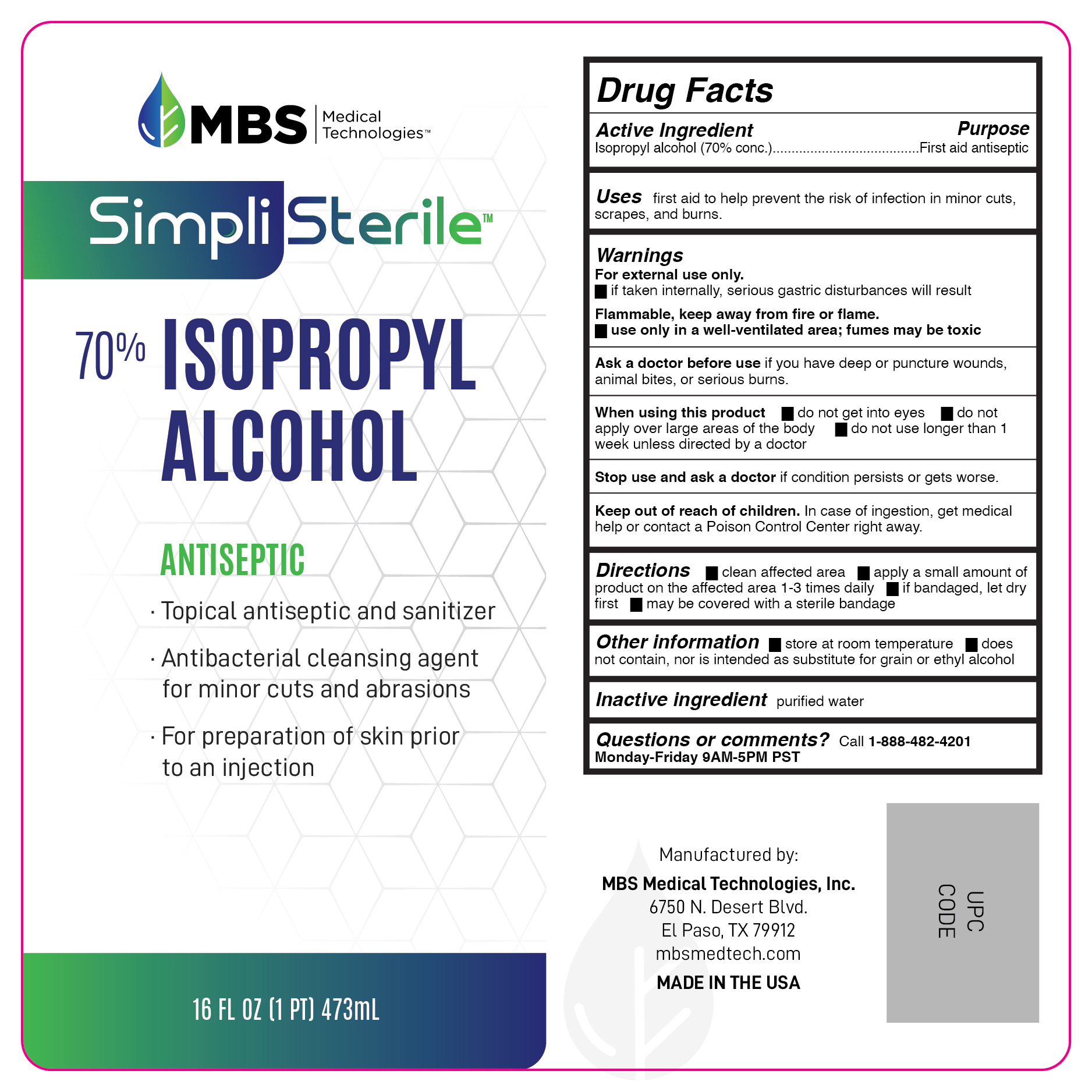 DRUG LABEL: 70% Isopropyl Alcohol
NDC: 79590-002 | Form: LIQUID
Manufacturer: MBS Medical Technologies Inc
Category: otc | Type: HUMAN OTC DRUG LABEL
Date: 20200915

ACTIVE INGREDIENTS: ISOPROPYL ALCOHOL 700 mg/1 mL
INACTIVE INGREDIENTS: WATER

70% Isopropyl Alcohol

active ingredient

Isopropyl Alcohol 70%

purpose

First Aid Antiseptic

use

First aid to help prevent the risk of infection in:

- minor cuts
- scrapes
- burns

warnings

For external use only. If taken internally serious gastric disturbances will result.

Flammable. Keep away from fire or flame, heat, spark, electrical

ask a doctor

if you have deep or puncture wounds, animal bites or serious burns

When using this product

- do not get into eyes
- do not inhale
- do not apply over large area of the body

Stop use and ask a doctor if

condition persists or gets worse

Keep out of reach of children.

If swallowed, get medical help or contact a Poison Control Center right away.

caution

Fumes can be acutely irritating to skin, eyes and the respiratory system. Do not apply to irritated skin or if excessive irritation develops. Avoid getting into the eyes or on mucous membranes. Avoid inhaling this product.

directions

- clean the affected area
- apply a small amount of this product on the affected area 1 to 3 times daily
- may be covered with a sterile bandage
- if bandaged, let dry first

Other information

- does not contain, nor is intended as a substitute for grain or ethyl alcohol

inactive ingredients

deionized water

Distributed by MBS Medical Technologies, Inc

6750 N Desert Blvd

El Paso, TX 79912

www.mbsmedtech.com

Questions: 888-482-4201

principal display panel

MBS Medical Technologies

70%

Isopropyl

Alcohol

First Aid Antiseptic

WARNING FLAMMABLE - Keep away from heat, spark, electrical, fire or flame

Ue only in a well-ventilated area;

fumes can be harmful

CAUTION: Do not point at others;

product will squirt when squeezed

16 FL OZ (473.2 mL)